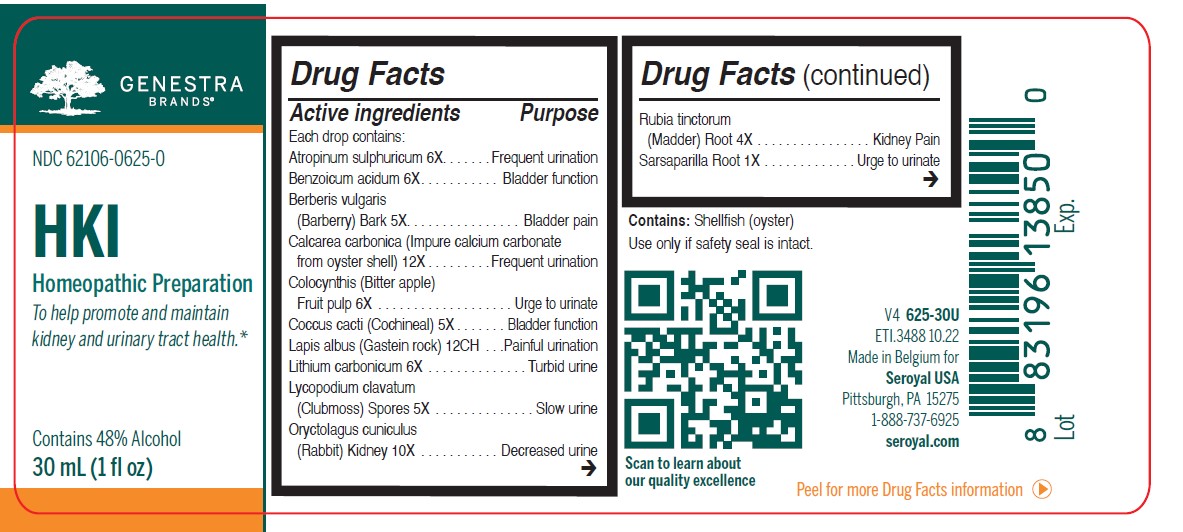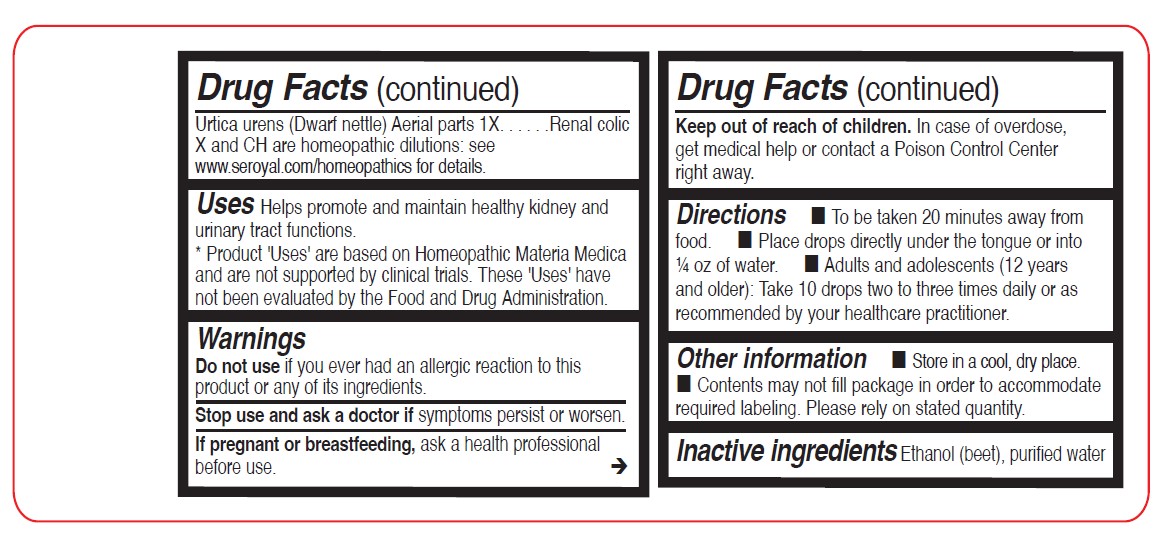 DRUG LABEL: HKI
NDC: 62106-0625 | Form: LIQUID
Manufacturer: Seroyal USA
Category: homeopathic | Type: HUMAN OTC DRUG LABEL
Date: 20230131

ACTIVE INGREDIENTS: ATROPINE SULFATE 6 [hp_X]/30 mL; OYSTER SHELL CALCIUM CARBONATE, CRUDE 12 [hp_X]/30 mL; CITRULLUS COLOCYNTHIS FRUIT PULP 6 [hp_X]/30 mL; LYCOPODIUM CLAVATUM SPORE 5 [hp_X]/30 mL; ORYCTOLAGUS CUNICULUS KIDNEY 10 [hp_X]/30 mL; SARSAPARILLA 1 [hp_X]/30 mL; CALCIUM HEXAFLUOROSILICATE 12 [hp_C]/30 mL; BENZOIC ACID 6 [hp_X]/30 mL; PROTORTONIA CACTI 5 [hp_X]/30 mL; LITHIUM CARBONATE 6 [hp_X]/30 mL; RUBIA TINCTORUM ROOT 4 [hp_X]/30 mL; URTICA URENS 1 [hp_X]/30 mL; BERBERIS VULGARIS ROOT BARK 5 [hp_X]/30 mL
INACTIVE INGREDIENTS: ALCOHOL; WATER

HKI

Active ingredients

Each drop contains:

Atropinum sulphuricum 6X

Benzoicum acidum 6X
Berberis vulgaris (Barberry) Bark 5X
Calcarea carbonica 12X
Colocynthis (Bitter apple) Dried fruit 6X

Coccus cacti (Cochineal) 5X

Lapis albus (Gastein rock) 12CH

Lithium carbonicum 6X
Lycopodium clavatum (Clubmoss) Spores 5X
Oryctolagus cuniculus (Rabbit) Kidney 10X

Rubia tinctorum (Madder) Root 4X
Sarsaparilla Root 1X

Urtica urens (Dwarf Nettle) Aerial parts 1X

Uses

Helps promote and maintain healthy kidney and urinary tract functions.

Warnings
Stop use and ask a doctor if symptoms persist or worsen.
If pregnant or breastfeeding, ask a health professional before use.
Keep out of reach of children.
In case of overdose, get medical help or contact a Poison Control Center right away.

Contains Shellfish (oyster)

Stop use and ask a doctor if symptoms persist or worsen.

PREGNANCY OR BREAST FEEDING

If pregnant or breastfeeding, ask a health professional before use.

Keep out of reach of children.

OVERDOSAGE

In case of overdose, get medical help or contact a Poison Control Center right away.

Inactive ingredients

Ethanol (beet), purified water

Other information

Store in a cool, dry place.

Contents may not fill package in order to accommodate required labeling. Please rely on stated quantity.

Use only if safety seal is intact.

Directions

To be taken 20 minutes away from food.

Place drops directly under the tongue or into ¼ oz of water.

Adults and adolescents (12 years and older): Take 10 drops two to three times daily or as recommended by your healthcare practitioner.

Children (under 12 years): Take under the direction of your healthcare practitioner.

Uses

Helps promote and maintain healthy kidney and urinary tract functions.

Directions

To be taken 20 minutes away from food.

Place drops directly under the tongue or into ¼ oz of water.

Adults and adolescents (12 years and older): Take 10 drops two to three times daily or as recommended by your healthcare practitioner.

Children (under 12 years): Take under the direction of your healthcare practitioner.

PACKAGE LABEL

Genestra Brands

NDC 62106-0625-0

HKI

HOMEOPATHIC PREPARATION

To help promote and maintain
kidney and urinary tract health.

Contains 48% Alcohol

1 fl oz (30 mL)